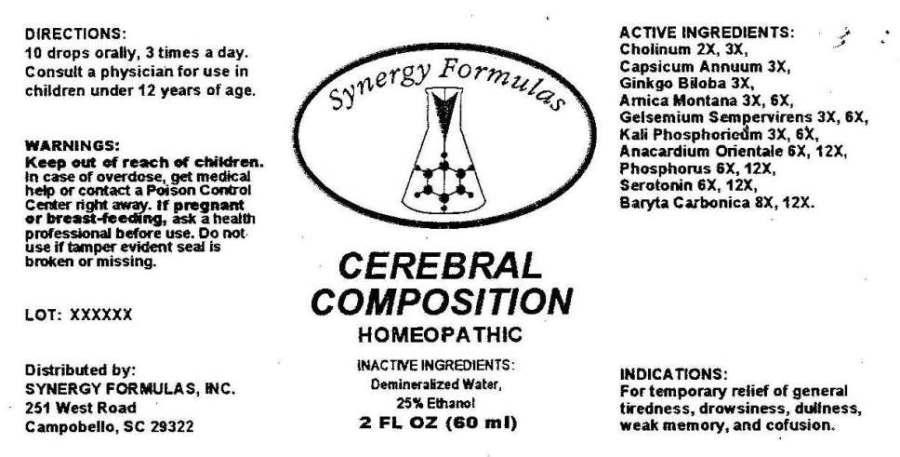 DRUG LABEL: Cerebral Composition
NDC: 43772-0036 | Form: LIQUID
Manufacturer: Synergy Formulas, Inc.
Category: homeopathic | Type: HUMAN OTC DRUG LABEL
Date: 20140716

ACTIVE INGREDIENTS: CHOLINE HYDROXIDE 2 [hp_X]/1 mL; CAPSICUM 3 [hp_X]/1 mL; GINKGO 3 [hp_X]/1 mL; ARNICA MONTANA 3 [hp_X]/1 mL; GELSEMIUM SEMPERVIRENS ROOT 3 [hp_X]/1 mL; POTASSIUM PHOSPHATE, DIBASIC 3 [hp_X]/1 mL; ANACARDIUM OCCIDENTALE FRUIT 6 [hp_X]/1 mL; PHOSPHORUS 6 [hp_X]/1 mL; SEROTONIN HYDROCHLORIDE 6 [hp_X]/1 mL; BARIUM CARBONATE 8 [hp_X]/1 mL
INACTIVE INGREDIENTS: WATER; ALCOHOL

DRUG FACTS:

ACTIVE INGREDIENTS:

Cholinum 2X, 3X, Capsicum Annuum 3X, Ginkgo Biloba 3X, Arnica Montana 3X, 6X, Gelsemium Sempervirens 3X, 6X, Kali Phosphoricum 3X, 6X, Anacardium Orientale 6X, 12X, Phosphorus 6X, 12X, Serotonin (Hydrochloride) 6X, 12X, Baryta Carbonica 8X, 12X

INDICATIONS:

For temporary relief of general tiredness, drowsiness, dullness, weak memory, and confusion.

WARNINGS:

Keep out of reach of children. In case of overdose, get medical help or contact a Poison Control Center right away.

If pregnant or breast-feeding, ask a health professional before use.

Do not use if tamper seal is broken or missing.

KEEP OUT OF REACH OF CHILDREN. In case of overdose, get medical help or contact a Poison Control Center right away.

DIRECTIONS:

10 drops orally, 3 times a day. Consult a physician for use in children under 12 years of age.

INDICATIONS:

For temporary relief of general tiredness, drowsiness, dullness, weak memory, and confusion.

INACTIVE INGREDIENTS:

Demineralized Water, 25% Ethanol

QUESTIONS:

Distributed by:

SYNERGY FORMULAS, INC

251 West Road

Campobello, SC 29322

PACKAGE LABEL DISPLAY:

Synergy Formulas

CEREBRAL COMPOSITION

HOMEOPATHIC

2 FL OZ (60 ml)